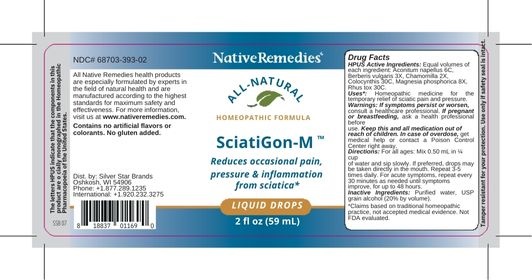 DRUG LABEL: NativeRemedies Sciatigon M
NDC: 68703-393 | Form: LIQUID
Manufacturer: Silver Star Brands
Category: homeopathic | Type: HUMAN OTC DRUG LABEL
Date: 20250101

ACTIVE INGREDIENTS: CITRULLUS COLOCYNTHIS FRUIT 30 [hp_C]/59 mL; MAGNESIUM PHOSPHATE, DIBASIC TRIHYDRATE 8 [hp_X]/59 mL; BERBERIS VULGARIS FRUIT 3 [hp_X]/59 mL; MATRICARIA RECUTITA 2 [hp_X]/59 mL; TOXICODENDRON RADICANS LEAF 30 [hp_C]/59 mL; ACONITUM NAPELLUS 6 [hp_C]/59 mL
INACTIVE INGREDIENTS: WATER; ALCOHOL

NativeRemedies® Sciatigon-M™

HPUS Active Ingredients

HPUS Active Ingrediens: Equal volumes of each ingredient: Aconitum napellus 6C, Berberis vulgaris 3X, Chamomilla 2X, Colocynthis 30C, Magnesia phosphorica 8X, Rhus tox 30C.

The letters HPUS indicate that the components in this product are officially monographed in the Homeopathic Pharmacopoeia of the United States.

Usess*

Uses*: Homeopathic medicine for the temporary relief of sciatic pain and pressure.

*Claims based on traditional homeopathic practice, not accepted medical evidence. Not FDA evaluated.

Warnings

Warnings: If symptoms persist or worsen, consult a healthcare professional. If pregnant or breastfeeding, ask a health professional before use. Keep this and all medication out of reach of children. In case of overdoes, get medical help or contact a Poison Control Center right away.

Directions

Directions: For all ages: Mix 0.50 mL in 1/4 cup of water and sip slowly. If preferred, drops may be taken directly in the mouth. Repeat 3-5 times daily. For acute symptoms, repeat every 30 minutes as needed unitl symptoms improve, for up to 48 hours.

OTHER SAFETY INFORMATION

Contains no artificial flavors or colorants. No gluten added.

Tample resistant for your protection. Use only if safety seal is intact.

Inactive Ingredients

Inactive Ingredients: Purified water, USP grain alcohol (20% by volume).

KEEP OUT OF REACH OF CHILDREN

Keep this and all medication out of reach of children. In case of overdose, get medical help or contact a Poison Control Center right away.

PREGNANCY OR BREAST FEEDING

If pregnant or breastfeeding, ask a health professional before use.

PURPOSE

Reduces occasional pain, pressure & inflammation for sciatica.